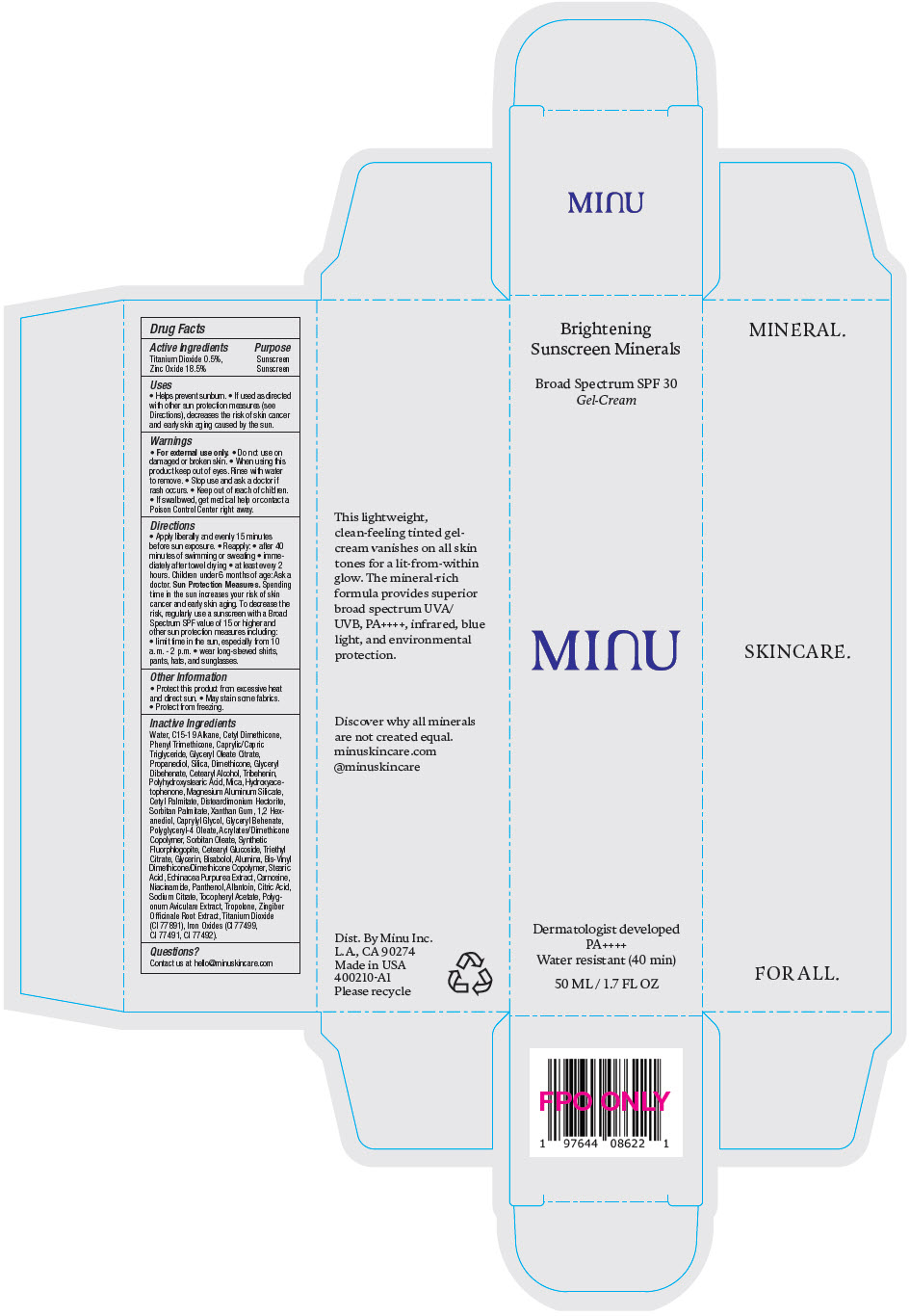 DRUG LABEL: Minu Brightening Sunscreen Minerals SPF 30
NDC: 84184-001 | Form: CREAM
Manufacturer: MINU
Category: otc | Type: HUMAN OTC DRUG LABEL
Date: 20240927

ACTIVE INGREDIENTS: TITANIUM DIOXIDE 5 mg/1 mL; ZINC OXIDE 185 mg/1 mL
INACTIVE INGREDIENTS: WATER; C15-19 ALKANE; PHENYL TRIMETHICONE; MEDIUM-CHAIN TRIGLYCERIDES; GLYCERYL MONOOLEATE CITRATE; PROPANEDIOL; SILICON DIOXIDE; DIMETHICONE; GLYCERYL DIBEHENATE; CETOSTEARYL ALCOHOL; TRIBEHENIN; MICA; HYDROXYACETOPHENONE; MAGNESIUM ALUMINUM SILICATE; CETYL PALMITATE; DISTEARDIMONIUM HECTORITE; SORBITAN MONOPALMITATE; XANTHAN GUM; 1,2-HEXANEDIOL; CAPRYLYL GLYCOL; POLYGLYCERYL-4 OLEATE; SORBITAN MONOOLEATE; MAGNESIUM POTASSIUM ALUMINOSILICATE FLUORIDE; CETEARYL GLUCOSIDE; TRIETHYL CITRATE; GLYCERIN; LEVOMENOL; ALUMINUM OXIDE; STEARIC ACID; ECHINACEA PURPUREA WHOLE; CARNOSINE; NIACINAMIDE; PANTHENOL; ALLANTOIN; CITRIC ACID MONOHYDRATE; SODIUM CITRATE, UNSPECIFIED FORM; .ALPHA.-TOCOPHEROL ACETATE; POLYGONUM AVICULARE TOP; TROPOLONE; GINGER; FERROSOFERRIC OXIDE; FERRIC OXIDE RED; FERRIC OXIDE YELLOW

Minu Brightening Sunscreen Minerals SPF 30

Drug Facts

ACTIVE INGREDIENT

Active Ingredients | Purpose
Titanium Dioxide 0.5%, | Sunscreen
Zinc Oxide 18.5% | Sunscreen

Uses

- Helps prevent sunburn.
- If used as directed with other sun protection measures (see Directions), decreases the risk of skin cancer and early skin aging caused by the sun.

Warnings

- For external use only.

- Do not use on damaged or broken skin.

- When using this product keep out of eyes. Rinse with water to remove.

- Stop use and ask a doctor if rash occurs.

- Keep out of reach of children.
- If swallowed, get medical help or contact a Poison Control Center right away.

Directions

- Apply liberally and evenly 15 minutes before sun exposure.
- Reapply:
  - after 40 minutes of swimming or sweating
  - immediately after towel drying
  - at least every 2 hours. Children under 6 months of age: Ask a doctor.

Sun Protection Measures

Spending time in the sun increases your risk of skin cancer and early skin aging. To decrease the risk, regularly use a sunscreen with a Broad Spectrum SPF value of 15 or higher and other sun protection measures including:

- limit time in the sun, especially from 10 a.m. - 2 p.m.
- wear long-sleeved shirts, pants, hats, and sunglasses.

Other Information

- Protect this product from excessive heat and direct sun.
- May stain some fabrics.
- Protect from freezing.

Inactive Ingredients

Water, C15-19 Alkane, Cetyl Dimethicone, Phenyl Trimethicone, Caprylic/Capric Triglyceride, Glyceryl Oleate Citrate, Propanediol, Silica, Dimethicone, Glyceryl Dibehenate, Cetearyl Alcohol, Tribehenin, Polyhydroxystearic Acid, Mica, Hydroxyacetophenone, Magnesium Aluminum Silicate, Cetyl Palmitate, Disteardimonium Hectorite, Sorbitan Palmitate, Xanthan Gum, 1,2 Hexanediol, Caprylyl Glycol, Glyceryl Behenate, Polyglyceryl-4 Oleate, Acrylates/Dimethicone Copolymer, Sorbitan Oleate, Synthetic Fluorphlogopite, Cetearyl Glucoside, Triethyl Citrate, Glycerin, Bisabolol, Alumina, Bis-Vinyl Dimethicone/Dimethicone Copolymer, Stearic Acid, Echinacea Purpurea Extract, Carnosine, Niacinamide, Panthenol, Allantoin, Citric Acid, Sodium Citrate, Tocopheryl Acetate, Polygonum Aviculare Extract, Tropolone, Zingiber Officinale Root Extract, Titanium Dioxide (CI 77891), Iron Oxides (CI 77499, CI 77491, CI 77492).

Questions?

Contact us at hello@minuskincare.com

Dist. By Minu Inc.
L.A., CA 90274

PRINCIPAL DISPLAY PANEL - 50 ML Bottle Carton

Brightening
Sunscreen Minerals

Broad Spectrum SPF 30
Gel-Cream

MINU

Dermatologist developed
PA++++
Water resistant (40 min)

50 ML / 1.7 FL OZ